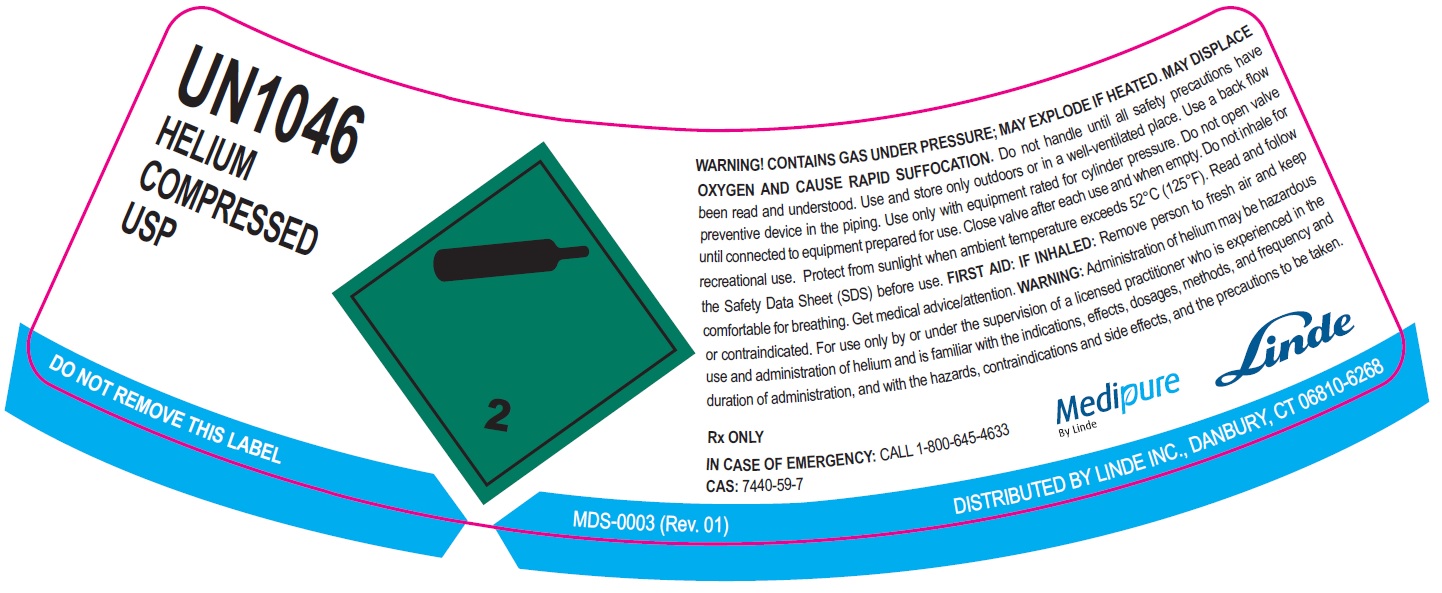 DRUG LABEL: Helium
NDC: 59579-005 | Form: GAS
Manufacturer: Linde Gas & Equipment Inc.
Category: prescription | Type: HUMAN PRESCRIPTION DRUG LABEL
Date: 20250115

ACTIVE INGREDIENTS: HELIUM 990 mL/1 L

Helium - Human

PACKAGE LABEL

UN1046 HELIUM, COMPRESSED USP

WARNING! CONTAINS GAS UNDER PRESSURE; MAY EXPLODE IF HEATED. MAY DISPLACE
OXYGEN AND CAUSE RAPID SUFFOCATION. Do not handle until all safety precautions have been read and understood.
Use and store only outdoors or in a well-ventilated place. Use a back flow preventive device in the piping.
Use only with equipment rated for cylinder pressure. Do not open valve until connected to equipment prepared for use.
Close valve after each use and when empty. Do not inhale for recreational use.
Protect from sunlight when ambient temperature exceeds 52°C (125°F). Read and follow the Safety Data Sheet (SDS) before use.
FIRST AID: IF INHALED: Remove person to fresh air and keep comfortable for breathing.
Get medical advice/attention. WARNING: Administration of helium may be hazardous or contraindicated.
For use only by or under the supervision of a licensed practitioner who is experienced in the use and administration of
helium and is familiar with the indications, effects, dosages, methods, and frequency and duration of administration,
and with the hazards, contraindications and side effects, and the precautions to be taken.

Rx ONLY

IN CASE OF EMERGENCY: CALL 1-800-645-4633

CAS: 7440-59-7

Medipure By Linde

Linde

DO NOT REMOVE THIS LABEL MDS-0003 (Rev. 01)

DISTRIBUTED BY LINDE INC., DANBURY, CT 06810-6268